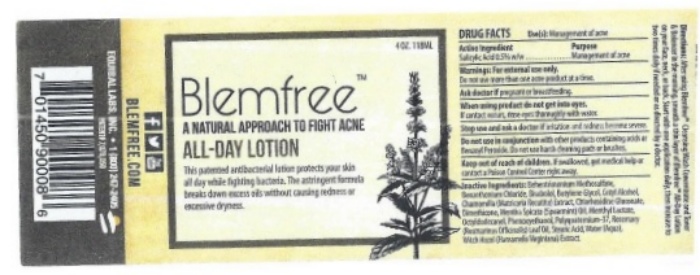 DRUG LABEL: BlemFree
NDC: 53228-002 | Form: LOTION
Manufacturer: Equibal, Inc.
Category: otc | Type: HUMAN OTC DRUG LABEL
Date: 20251217

ACTIVE INGREDIENTS: SALICYLIC ACID 0.587 g/118 mL
INACTIVE INGREDIENTS: BUTYLENE GLYCOL; CETYL ALCOHOL; BEHENTRIMONIUM METHOSULFATE; BENZETHONIUM CHLORIDE; LEVOMENOL; CHLORHEXIDINE GLUCONATE; DIMETHICONE; MATRICARIA RECUTITA; MENTHYL LACTATE, (-)-; OCTYLDODECANOL; PHENOXYETHANOL; POLYQUATERNIUM-37 (25000 MPA.S); STEARIC ACID; WATER; WITCH HAZEL; HAMAMELIS VIRGINIANA TOP

Blem Free

Drug Facts Active Ingredient

Salicylic Acid 0.5% w/w

Purpose

Management of Acne

Keep out of reach of children.

If swallowed, get medical help or contact a Poison Control Center right away.

Uses

Acne

Warnings

For external use only

Ask a doctor if

pregnant or breastfeeding

When using this product do not get into eyes.

if contact occurs, rinse eyes thoroughly with water

Stop use and ask a doctor if

irritation and redness become severe

Do not use in conjunction

conjunctionwith other products containing acids or Benzoyl Peroxide. Do use harsh cleaning pads or brushes.

Directions

After using Blemfree™ Cleansing WashConcentrate and Toner & Balancer in the morning, smooth a thin layer of Blemfree™ All-Day Lotion on your face, neck, or back. Start with one application daily, then increase to two times daily if needed or as directed by a doctor.

Inactive Ingredients

Behentrimonium Methosulfate, Benzethonium Chloride, Bisabolol, Butylene Glycol, Cetyl Alcohol, Chamomilla (Metricarla Recutia) Extract, Chlorhexidine Gluconate, Dimethicone, Mentha Spicata (Spearmint) Oil, Menthyl Lactate, Octyldodecanol, Phenoxyethanol, Polyquatemium-37, Rosemary (Rosmarinus Officinalis) Leaf Oil, Stearic Acid, Water (Aqua), Witch Hazel (Hamamelis Virginiana) Extract.

BlemFree Product Label

BLEMFREE.COM; EQUIBAL LABS, INC. ●1 (800) 247-2405; PATENT# 7,078,050 | 4 OZ. 118ML; Blemfree ™; A NATURAL APPROACH TO FIGHT ACNE; This patented antibacterial lotion protects our skin all while fighting bacteria. The astringent formula breaks down excess oils without causing redness or excessive dryness. | DRUG FACTSUse(s): Management of acne; Active Ingredient Purpose; Salicylic Acid 0.5% w/w Management of Acne; Warnings: For external use only.; Do not use more than one acne product at a time.; Ask doctor ifpregnant or breastfeeding; When using product do not get into eyes.; If contact occurs, rinse eyes thoroughly with water.; Stop use and ask a doctor ifirritation and redness become severe.; Do not use in conjunctionwith other products containing acids or Benzoyl Peroxide. Do use harsh cleaning pads or brushes.; Keep out of reach of children.If swallowed, get medical help or contact a Poison Control Center right away.; Inactive Ingredients:Behentrimonium Methosulfate, Benzethonium Chloride, Bisabolol, Butylene Glycol, Cetyl Alcohol, Chamomilla (Metricarla Recutia) Extract, Chlorhexidine Gluconate, Dimethicone, Mentha Spicata (Spearmint) Oil, Menthyl Lactate, Octyldodecanol, Phenoxyethanol, Polyquatemium-37, Rosemary (Rosmarinus Officinalis) Leaf Oil, Stearic Acid, Water (Aqua), Witch Hazel (Hamamelis Virginiana) Extract. | Directions:After using Blemfree™ Cleansing WashConcentrate and Toner & Balancer in the morning, smooth a thin layer of Blemfree™ All-Day Lotion on your face, neck, or back. Start with one application daily, then increase to two times daily if needed or as directed by a doctor.
 | 4 OZ. 118ML; Blemfree ™; A NATURAL APPROACH TO FIGHT ACNE; This patented antibacterial lotion protects our skin all while fighting bacteria. The astringent formula breaks down excess oils without causing redness or excessive dryness. | DRUG FACTSUse(s): Management of acne; Active Ingredient Purpose; Salicylic Acid 0.5% w/w Management of Acne; Warnings: For external use only.; Do not use more than one acne product at a time.; Ask doctor ifpregnant or breastfeeding; When using product do not get into eyes.; If contact occurs, rinse eyes thoroughly with water.; Stop use and ask a doctor ifirritation and redness become severe.; Do not use in conjunctionwith other products containing acids or Benzoyl Peroxide. Do use harsh cleaning pads or brushes.; Keep out of reach of children.If swallowed, get medical help or contact a Poison Control Center right away.; Inactive Ingredients:Behentrimonium Methosulfate, Benzethonium Chloride, Bisabolol, Butylene Glycol, Cetyl Alcohol, Chamomilla (Metricarla Recutia) Extract, Chlorhexidine Gluconate, Dimethicone, Mentha Spicata (Spearmint) Oil, Menthyl Lactate, Octyldodecanol, Phenoxyethanol, Polyquatemium-37, Rosemary (Rosmarinus Officinalis) Leaf Oil, Stearic Acid, Water (Aqua), Witch Hazel (Hamamelis Virginiana) Extract. | Directions:After using Blemfree™ Cleansing WashConcentrate and Toner & Balancer in the morning, smooth a thin layer of Blemfree™ All-Day Lotion on your face, neck, or back. Start with one application daily, then increase to two times daily if needed or as directed by a doctor.

Blemfree™ ALL DAY LOTION VISIT BLEMFREE.COM

For an explanation of our ingredients.

DRUG FACTS Use(s): Management of acne

Active Ingredient Purpose

Salicylic Acid 0.5% w/w Management of Acne

Warnings: For external use only.

Do not use more than one acne product at a time.

Ask doctor ifpregnant or breastfeeding

When using product do not get into eyes.

If contact occurs, rinse eyes thoroughly with water.

Stop use and ask a doctor ifirritation and redness become severe.

Do not use in conjunctionwith other products containing acids or Benzoyl Peroxide. Do use harsh cleaning pads or brushes.

Keep out of reach of children.If swallowed, get medical help or contact a Poison Control Center right away.

Inactive Ingredients:Behentrimonium Methosulfate, Benzethonium Chloride, Bisabolol, Butylene Glycol, Cetyl Alcohol, Chamomilla (Metricarla Recutia) Extract, Chlorhexidine Gluconate, Dimethicone, Mentha Spicata (Spearmint) Oil, Menthyl Lactate, Octyldodecanol, Phenoxyethanol, Polyquatemium-37, Rosemary (Rosmarinus Officinalis) Leaf Oil, Stearic Acid, Water (Aqua), Witch Hazel (Hamamelis Virginiana) Extract.

Questions or Comments?Call us toll free at 1(800)247-2405. Tuesday-Friday 8AM-6PM ET.

Equibal Labs®, PO Box 180, Unionville, NY 10988. Retain this insert for directions and information.